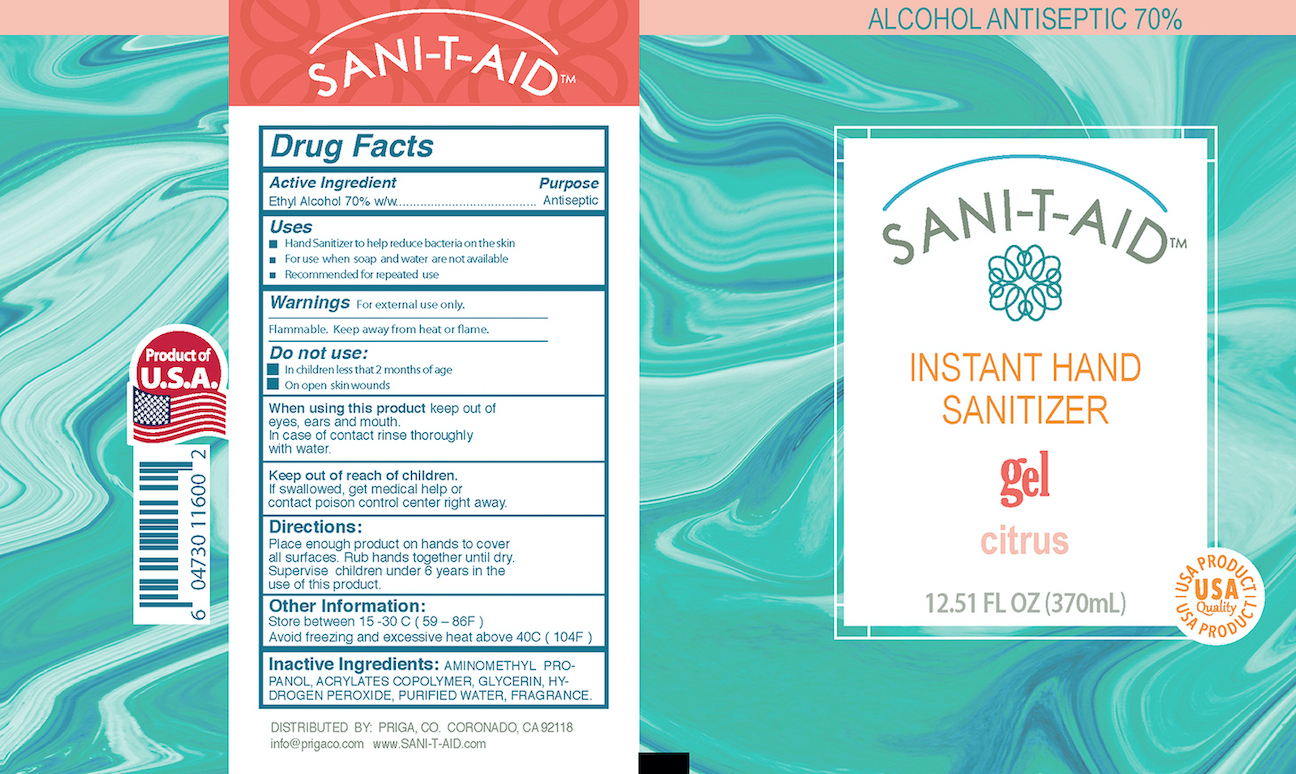 DRUG LABEL: Hand Sanitizer
NDC: 78319-008 | Form: GEL
Manufacturer: Pafer Foods & Beverages, S. de R.L de C.V.
Category: otc | Type: HUMAN OTC DRUG LABEL
Date: 20200727

ACTIVE INGREDIENTS: ALCOHOL 70 mL/100 mL
INACTIVE INGREDIENTS: HYDROGEN PEROXIDE; METHACRYLIC ACID - ETHYL ACRYLATE COPOLYMER (4500 MPA.S); GLYCERIN; AMINOMETHYLPROPANOL; WATER; LIMONENE, (+)-

Citrus gel

ACTIVE INGREDIENT

Ethyl alcohol 70% v/v

PURPOSE

Antiseptic

INDICATIONS AND USAGE

- Hand Sanitizer to help reduce bacteria on the skin
- For use when soap and water are not available
- Recommended for repeated use

WARNINGS

For external use only

Flammable. Keep away from heat or flame

Do not use:

- In children less than 2 months of age
- On open skin wounds

Keep out of reach of children.

If swallowed, get medical help or contact poison control center right away.

Directions:

Place enough product on hands to cover all surfaces. Rub hands together until dry. Supervise children under 6 years in the use of this product.

OTHER SAFETY INFORMATION

Store between 15-30C (59-86F)

Avoid freezing and excessive heat above 40C (104F)

INACTIVE INGREDIENT

Aminoethyl Propanol, Acrylates Copolymer, Glycerin, Hydrogen Peroxide, Purified Water, Fragrance